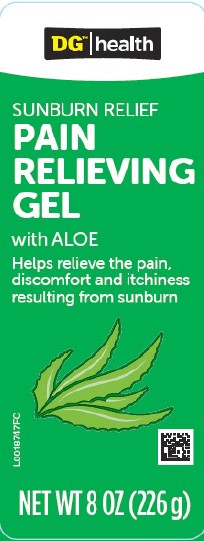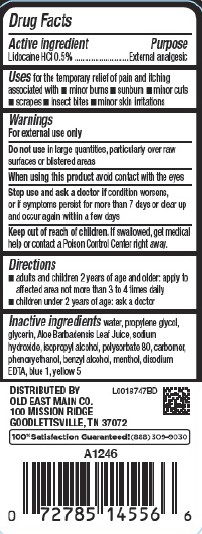 DRUG LABEL: Sunburn Relief
NDC: 55910-177 | Form: GEL
Manufacturer: Old East Main Co.
Category: otc | Type: HUMAN OTC DRUG LABEL
Date: 20260302

ACTIVE INGREDIENTS: LIDOCAINE HYDROCHLORIDE 5 mg/1 g
INACTIVE INGREDIENTS: WATER; PROPYLENE GLYCOL; GLYCERIN; ALOE VERA LEAF; SODIUM HYDROXIDE; ISOPROPYL ALCOHOL; POLYSORBATE 80; CARBOMER HOMOPOLYMER, UNSPECIFIED TYPE; PHENOXYETHANOL; BENZYL ALCOHOL; MENTHOL; EDETATE DISODIUM ANHYDROUS; FD&C BLUE NO. 1; FD&C YELLOW NO. 5

Dollar General 005.003/005AE
Sunburn Relief Gel

Active ingredient

Lidocaine HCl 0.5%

Purpose

External analgesic

Uses

for the temporary relief of pain and itching associated with

- minor burns
- sunburn
- minor cuts
- scrapes
- insect bites
- minor skin irritations

Warnings

For external use only

Do not use

in large quantities, particularly over raw surfaces or blistered areas

When using this product

avoid contact with the eyes

Stop use and ask a doctor if

condition worsens, or if symptoms persist for more than 7 days or clear up and occur again within a few days

Keep out of reach of children.

If swallowed, get medical help or contact a Poison Control Center right away.

Directions

- adults and children 2 years of age and older: apply to affected area not more than 3 to 4 times daily
- children under 2 years of age: ask a doctor

Inactive ingredients

water, propylene glycol, glycerin, Aloe Barbadensis Leaf Juice, sodium hydroxide, isopropyl alcohol, polysorbate 80, carbomer, phenoxyethanol, benzyl alcohol, menthol, disodium EDTA, blue 1, yellow 5

Adverse reaction

Distributed By

Old East Main Co.

100 MISSION RIDGE,

GOODLETTSVILLE, TN 37072

100% Satisfction Guaranteed! (888)309-9030

principal display panel

DG™|health

SUNBURN RELIEF

PAIN RELIEVING GEL

with ALOE

Helps relieve the pain, discomfort and itchiness resulting from sunburn

NET WT 8 OZ (226 g)